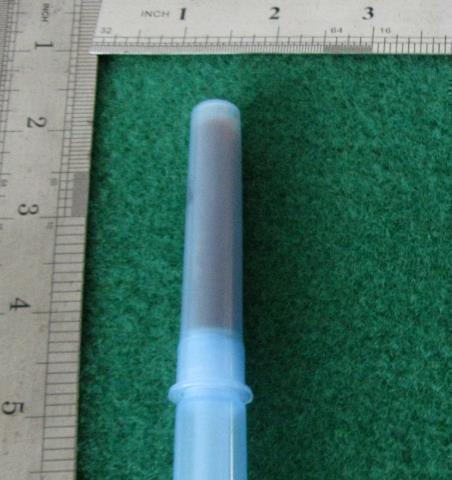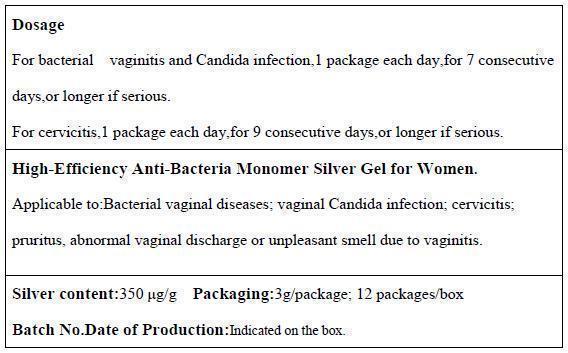 DRUG LABEL: Shuifulan High-Efficiency Anti-Bacteria Monomer Silver Gel for Women
NDC: 69519-0101 | Form: GEL, DENTIFRICE
Manufacturer: SHUIFULAN (BEIJING) BIOLOGICAL TECHNOLOGY CO., LTD
Category: homeopathic | Type: HUMAN OTC DRUG LABEL
Date: 20150109

ACTIVE INGREDIENTS: Silver 350 ug/3 g
INACTIVE INGREDIENTS: Carbomer 934 6 mg/3 g; Water 293650 ug/3 g

SHUIFULAN GEL

Active ingredient

Silver content: 350 μg/g; 4200 μg/package

Purpose

Anti-Bacteria

Monomer silver gel is a highly active agent which significantly suppresses and eliminates Candida albicans, Escherichia coli, Staphylococcus aureus and Pseudomonas aeruginosa within and around the vagina, prevents and cures inflammation, accelerates the recovery of wounds and lesioned tissues regardless of vagina pH without affecting normal vaginal bacteria.

When using

Indication to bacterial vaginal diseases; vaginal candida infection; cervicitis; pruritus; abnormal vaginal discharge, or unpleasant smell due to vaginitis.

Topical use: Apply on the affected area of vagina.

For bacterial vaginitis and candida infection, 1 package each day, for 7 consecutive days, or longer if serious.

For cervicitis, 1 package each day, for 9 consecutive days, or longer if serious.

Do not use if allergic to silver.

And it is not for virgins.

Notes:

1, Pregnant women or women in period avoid application in deep part of vagina.

2, Do not use if package is broken; do not use with medicine that contains Vaseline, chlorine, iodine or hydrogen peroxide.

Stop use

Stop use when finding any unpleasant symptoms.

Ask doctor

Ask doctor before you sure it is safe to your body.

Ask doctor/pharmacist when you current use other drugs.

Keep out of reach of children. If the product is swallowed, get medical help or contact a Poison Control Center right away.

Questions

Please contact us when you have any questions.

Pregnancy or breast feeding

Pregnant or breast feeding women shall follow doctor advice.

Indications & usage

Indication to bacterial vaginal diseases; vaginal candida infection; cervicitis; pruritus; abnormal vaginal discharge, or unpleasant smell due to vaginitis.

Topical use: Apply on the affected area of vagina.

Dosage & administration

For bacterial vaginitis and candida infection, 1 package each day, for 7 consecutive days, or longer if serious.
For cervicitis, 1 package each day, for 9 consecutive days, or longer if serious.

Dosage forms & strengths

Dosage form is Gel

Strengths is 3g(3mL)/tube

Warnings and precautions

Contraindications:

1, For external use only.

2, Not for virgins.

3, Do not use if allergic to silver.

4, Pregnant women shall follow doctor advice.

Notes:

1, Pregnant women or women in period avoid application in deep part of vagina.

2, Do not use if package is broken; do not use with medicine that contains Vaseline, chlorine, iodine or hydrogen peroxide.

3, This product is for external use only; do not take in. The gel may change in color, which is normal and has no impact on its effects.

4, Keep away from clothes to prevent contamination. Sanitary napkin is recommended to absorb the fluid of gel from vagina.

Package label. Principal display panel

Container Label

Package Label

Inactive ingredient

Carbomer 934 content: 6 mg/g; 72 mg/package

Water content: 293650 μg/g; 3523800 μg/package